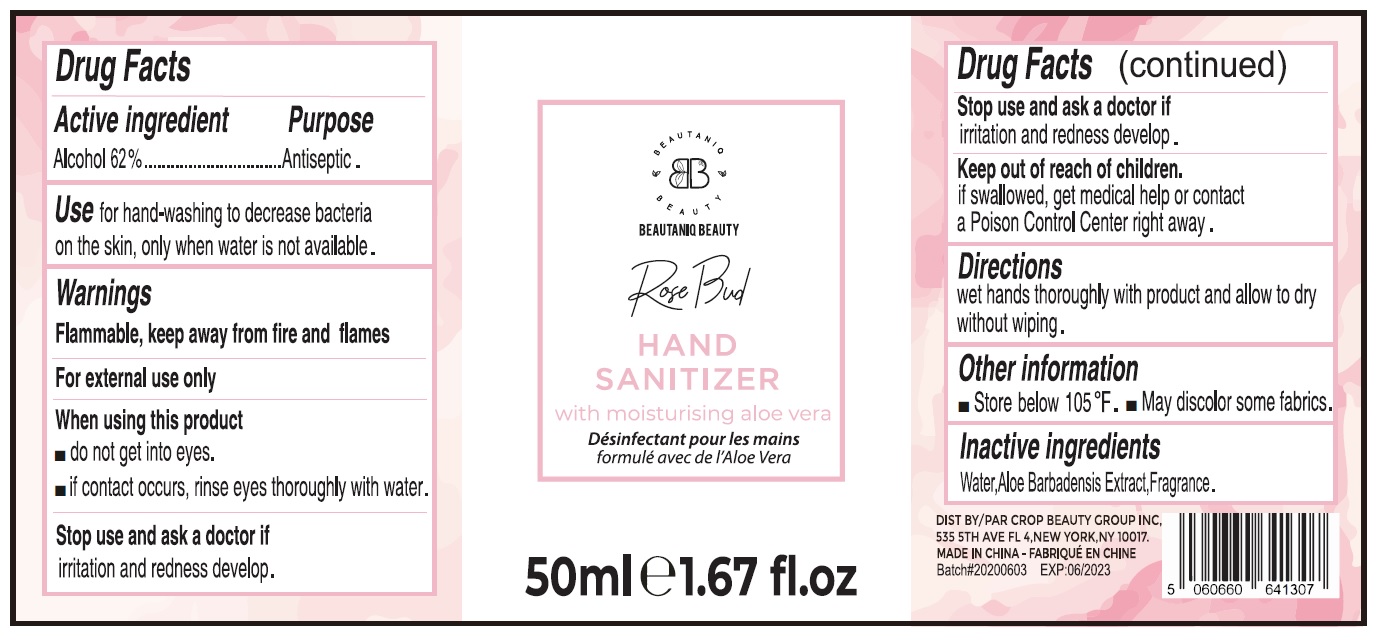 DRUG LABEL: BEAUTANIQ BEAUTY HAND SANITIZER
NDC: 78768-001 | Form: SPRAY
Manufacturer: CROP BEAUTY GROUP INC.
Category: otc | Type: HUMAN OTC DRUG LABEL
Date: 20231026

ACTIVE INGREDIENTS: ALCOHOL 0.62 mL/1 mL
INACTIVE INGREDIENTS: WATER

BEAUTANIQ BEAUTY HAND SANITIZER

Active ingredient

Alcohol 62%

Purpose

Antiseptic.

Use

for hand-washing to decrease bacteria on the skin, only when water is not available.

Warnings

Flammable, keep away from fire and flames

For external use only

When using this product

- do not get into eyes.
- if contact occurs, rinse eyes thoroughly with water.

Stop use and ask a doctor if

irritation and redness develop.

Keep out of reach of children.

if swallowed, get medical help or contact a Poison Control Center right away.

Directions

wet hands thoroughly with product and allow to dry without wiping.

Other information

- Store below 105 °F.
- May discolor some fabrics.

Inactive ingredients

Water,Aloe Barbadensis Extract,Fragrance.